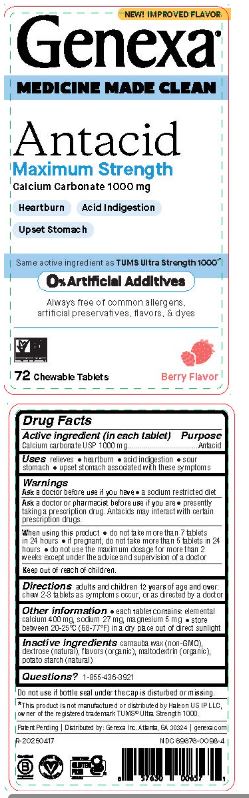 DRUG LABEL: Genexa Antacid Maximum Strength
NDC: 84998-0098 | Form: TABLET, CHEWABLE
Manufacturer: PNP Pharmaceuticals Inc
Category: otc | Type: HUMAN OTC DRUG LABEL
Date: 20250831

ACTIVE INGREDIENTS: CALCIUM CARBONATE 1000 mg/1 1
INACTIVE INGREDIENTS: CARNAUBA WAX; MALTODEXTRIN; DEXTROSE; STARCH, POTATO

Directions

adults and children 12 years of age and over: chew 2-3 tablets as symptoms occur, or as directed by a doctor

Other information

- each tablet contains: elemental calcium 400 mg, sodium 27 mg, magnesium 5 mg
- store between 20-25°C (68-77 °F) in a dry place out of direct sunlight

Inactive ingredients

carnauba wax (non-GMO), dextrose (natural), flavors (organic), maltodextrin (organic), potato starch (natural)

Questions? 1-855-436-3921

Do not use if bottle seal under the cap is disturbed or missing.

*This product is not manufactured or distributed by Haleon US IP LLC, owner of the registered trademark TUMS® Ultra Strength 1000.

Patent Pending | Distributed by: Genexa Inc. Atlanta, GA 30324 | genexa.com

NDC 69676-0098-4

Warnings

Ask a doctor before use if you have

- a sodium restricted diet

Ask a doctor or pharmacist before use if you are

- presently taking a prescription drug. Antacids may interact with certain prescription drugs.

When using this product

- do not take more than 7 tablets in 24 hours
- if pregnant, do not take more than 5 tablets in 24 hours
- do not use the maxium dosage for more than 2 weeks except under the advice and supervision of a doctor

Keep out of each of children

Drug Facts

Active ingredient (in each tablet)

Calcium carbonate USP 1000 mg

Purpose

Antacid

INDICATIONS AND USAGE

Uses relieves

- heartburn
- acid indigestion
- sour stomach
- upset stomach associated with these symptoms

PACKAGE LABEL

NEW! IMPROVED FLAVOR

Genexa®

MEDICINE MADE CLEAN

Antacid Maximum Strength

Calcium carbonate 1000 mg

Heartburn

Acid Indigestion

Upset Stomach

Same active ingredient as TUMS Ultra Strength 1000*

0% Artificial Additives

Always free of common allergens, artificial preservatives, flavors, & dyes

72 Chewable Tablets

Berry Flavor